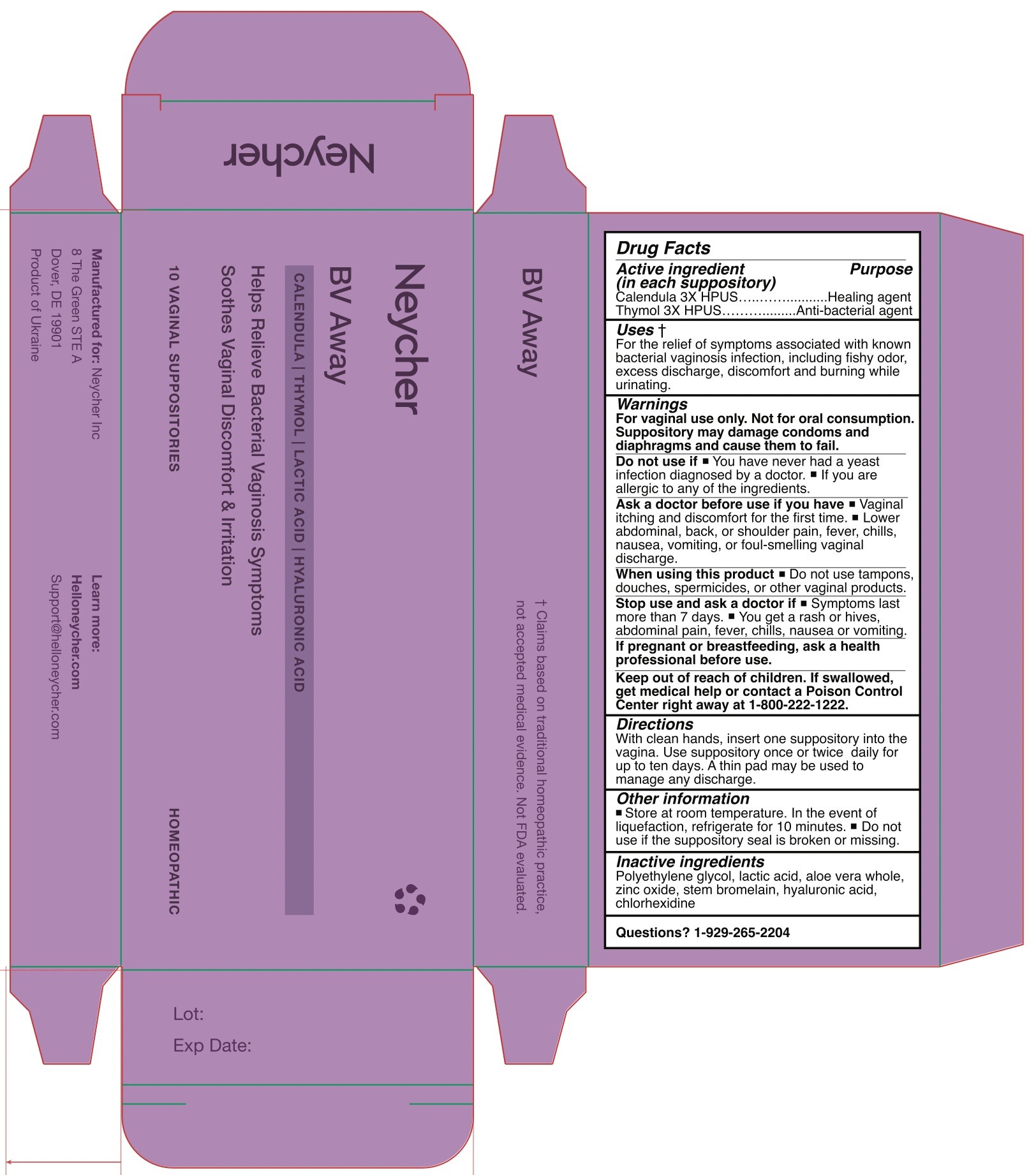 DRUG LABEL: Neycher BV Away
NDC: 84669-111 | Form: SUPPOSITORY
Manufacturer: NEYCHER INC
Category: homeopathic | Type: HUMAN OTC DRUG LABEL
Date: 20241105

ACTIVE INGREDIENTS: THYMOL 3 [hp_C]/1 1; CALENDULA OFFICINALIS FLOWERING TOP 3 [hp_C]/1 1
INACTIVE INGREDIENTS: ZINC OXIDE; LACTIC ACID; ALOE VERA WHOLE; CHLORHEXIDINE; POLYETHYLENE GLYCOL 1500; STEM BROMELAIN; HYALURONIC ACID

Neycher BV Away

Active Ingredient(s)

Calendula 3X HPUS.......Healing agent
Thymol 3X HPUG......... ..Anti-bacterial agent

Purpose

Healing agent
Anti-bacterial agent

Use

For the relief of symptoms associated with known bacterial vaginosis infection, including fishy odor, excess discharge, discomfort and burning while urinating.

Warnings

For vaginal use only. Not for oral consumption.

Suppository may damage condoms and
diaphragms and cause them to fail.

Do not use if ™ You have never had a yeast
infection diagnosed by a doctor. ™ If you are
allergic to any of the ingredients.

Ask a doctor before use if you have ® Vaginal
itching and discomfort for the first time. = Lower
abdominal, back, or shoulder pain, fever, chills,
nausea, vomiting, or foul-smelling vaginal
discharge.

When using this product = Do not use tampons,
douches, spermicides, or other vaginal products.
Stop use and ask a doctor if = Symptoms last
more than 7 days. ™ You get a rash or hives,
abdominal pain, fever, chills, nausea or vomiting.
If pregnant or breastfeeding, ask a health
professional before use.

Keep out of reach of children. If swallowed,
get medical help or contact a Poison Control
Center right away at 1-800-222-1222.

Directions

With clean hands, insert one suppository into the
vagina. Use suppository once or twice daily for
up to ten days. A thin pad may be used to
manage any discharge.

Other information

Store at room temperature.

In the event of liquefaction, refrigerate for 10 minutes.

Do not use if the suppository seal is broken or missing

Inactive ingredients

Polyethylene glycol, lactic acid, aloe vera whole,
zinc oxide, stem bromelain, hyaluronic acid,
chlorhexidine

Questions? 1-929-265-2204

Package Label - Principal Display Panel

NDC: 84669-111-11